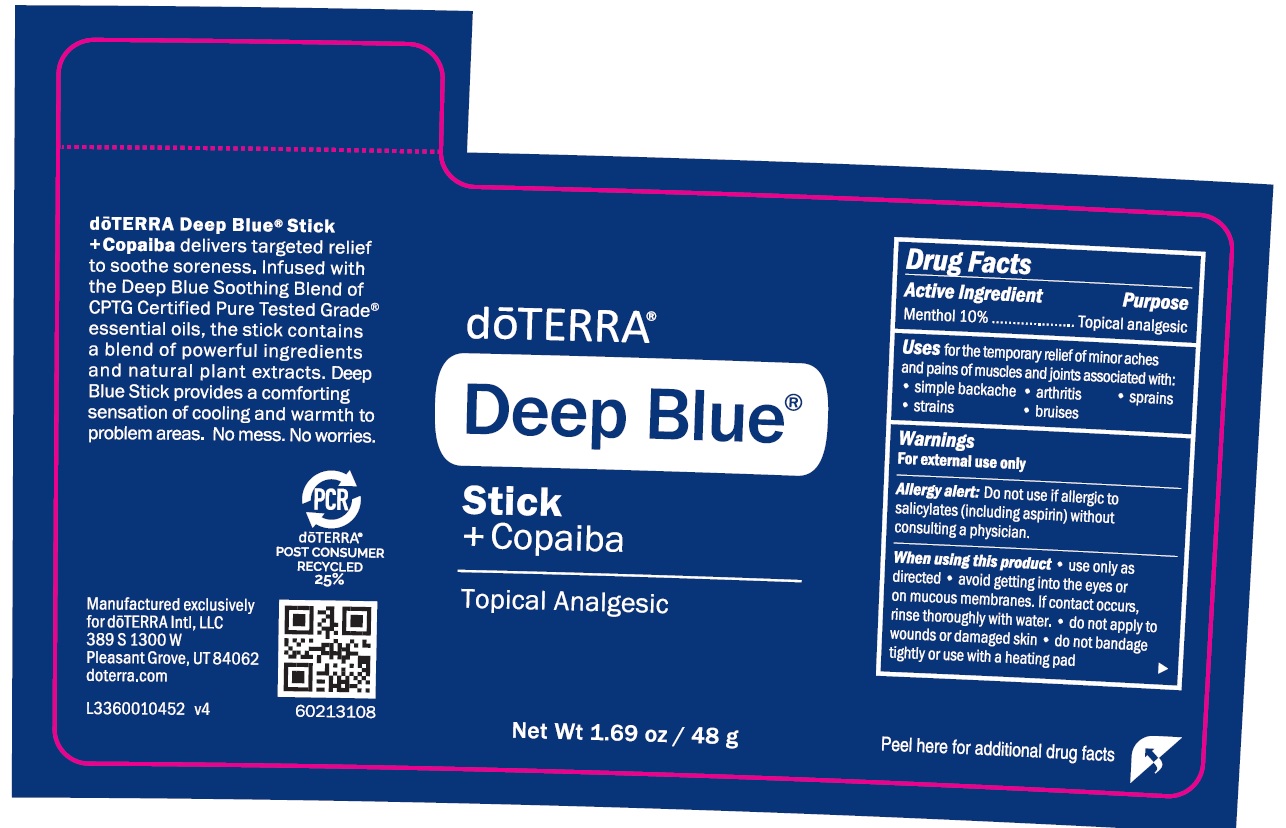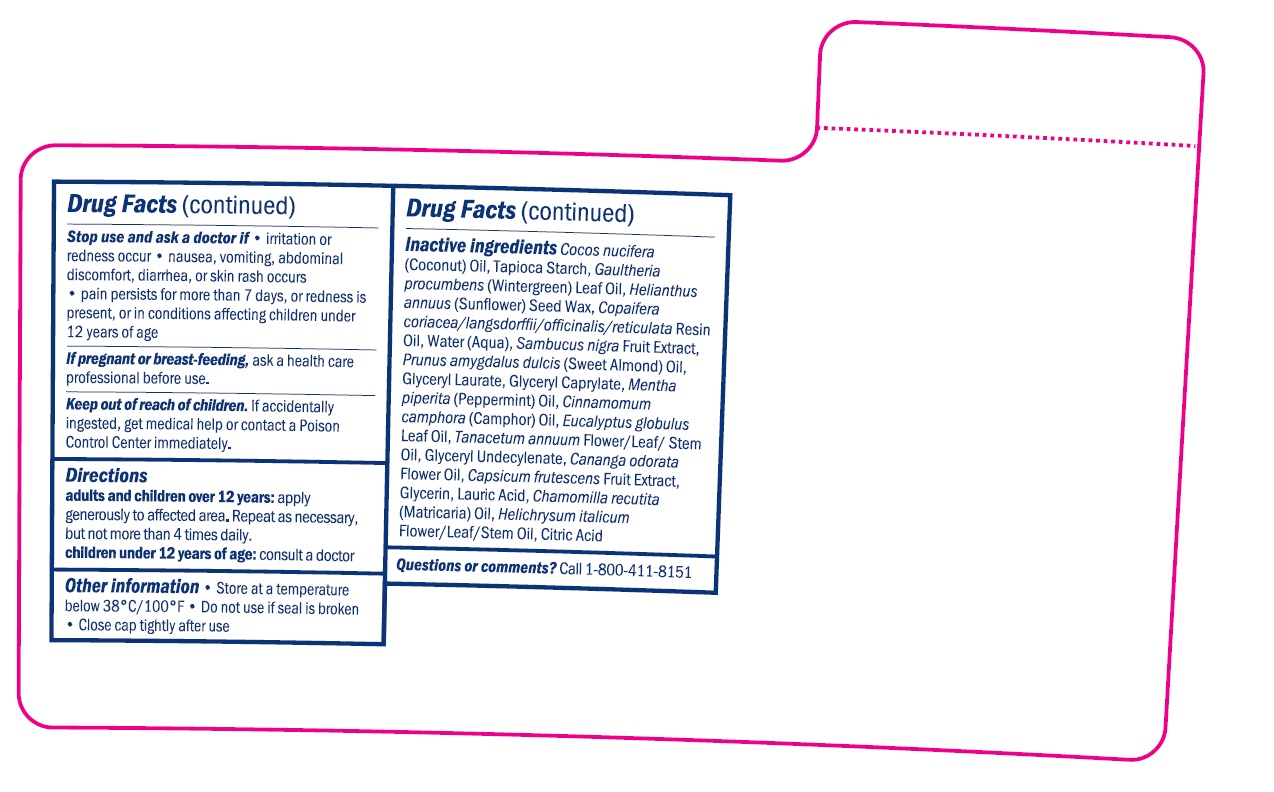 DRUG LABEL: Deep Blue
NDC: 71630-169 | Form: STICK
Manufacturer: doTERRA International, LLC
Category: otc | Type: HUMAN OTC DRUG LABEL
Date: 20250128

ACTIVE INGREDIENTS: MENTHOL 10 g/100 g
INACTIVE INGREDIENTS: GLYCERIN; ALMOND OIL; HELICHRYSUM ITALICUM FLOWER OIL; EUCALYPTUS GLOBULUS LEAF; GLYCERYL 1-UNDECYLENATE; CANANGA OIL; CAPSICUM FRUTESCENS WHOLE; MATRICARIA CHAMOMILLA FLOWERING TOP OIL; LAURIC ACID; WATER; COPAIBA OIL; PEPPERMINT OIL; GAULTHERIA PROCUMBENS LEAF; HELIANTHUS ANNUUS SEED WAX; COCONUT OIL; TANACETUM ANNUUM FLOWERING TOP OIL; SAMBUCUS NIGRA SUBSP. CERULEA FRUIT; GLYCERYL LAURATE; GLYCERYL CAPRYLATE; CAMPHOR OIL

Deep Blue Stick (TwinCraft)

Active Ingredient

Menthol 10%

PURPOSE

Topical analgesic

INDICATIONS AND USAGE

Uses for the temporary relief of minor aches and pains of muscles and joints associated with:

Simple backache

Arthritis

Sprains

Strains

Bruises

WARNINGS

For external use only

Allergy alert: Do not use if allergic to salicylates (including aspirin) without consulting a physician.

When using this product - use only as directed - avoid getting into the eyes or on mucous membranes. If contact occurs, rinse thoroughly with water - do not apply to wounds or damaged skin - do not bandages tightly or use with a heating pad.

PREGNANCY OR BREAST FEEDING

If pregnant or breast-feeding, ask a health care professional before use.

Keep out of reach of children.

If swallowed, get medical help or contact a Poison Control Center right away.

Stop use and ask a doctor if

• irritation or redness occur

• nausea, vomiting, abdominal discomfort, diarrhea, or skin rash occurs

• If pain persists for more than 7 days, or redness is present, or in conditions affecting children under 12 years of age

INSTRUCTIONS FOR USE

Adults and Children 12 years of age and older:

• apply generously to affected area

• repeat as necessary, but not more than 3 to 4 times daily

Children Under 12 years of Age: consult a doctor

Other information • Store at a temperature below 38c / 100f

•Do not use if seal is broken. • Close cap tightly after use.

INACTIVE INGREDIENT

Cocos Nucifera (Coconut) Oil, Tapioca Starch, Gaultheria Procumbens (Wintergreen) Leaf Oil, Helianthus Annuus (Sunflower) Seed Wax, Copaifera Coriacea/Langsdorffii/Officinalis/Reticulata Resin Oil, Water (Aqua), Sambucus Nigra Fruit Extract, Prunus Amygdalus Dulcis (Sweet Almond) Oil, Glyceryl Laurate, Glyceryl Caprylate, Mentha Piperita (Peppermint) Oil, Cinnamomum Camphora (Camphor) Oil, Eucalyptus Globulus Leaf Oil, Tanacetum Annuum Flower/Leaf/Stem Oil, Glyceryl Undecylenate, Cananga Odorata Flower Oil, Capsicum Frutescens Fruit Extract, Glycerin, Lauric Acid, Citric Acid, Chamomilla Recutita (Matricaria) Oil, Helichrysum Italicum Flower/Leaf/Stem Oil

Questions? 1-800-411-8151

DOSAGE AND ADMINISTRATION

Menthol 10%…..............................................Topical analgesic

PACKAGE LABEL

doTERRA Deep Blue Stick + Copaiba

Topical Analgesic

Net wt. 1.69 oz/48g